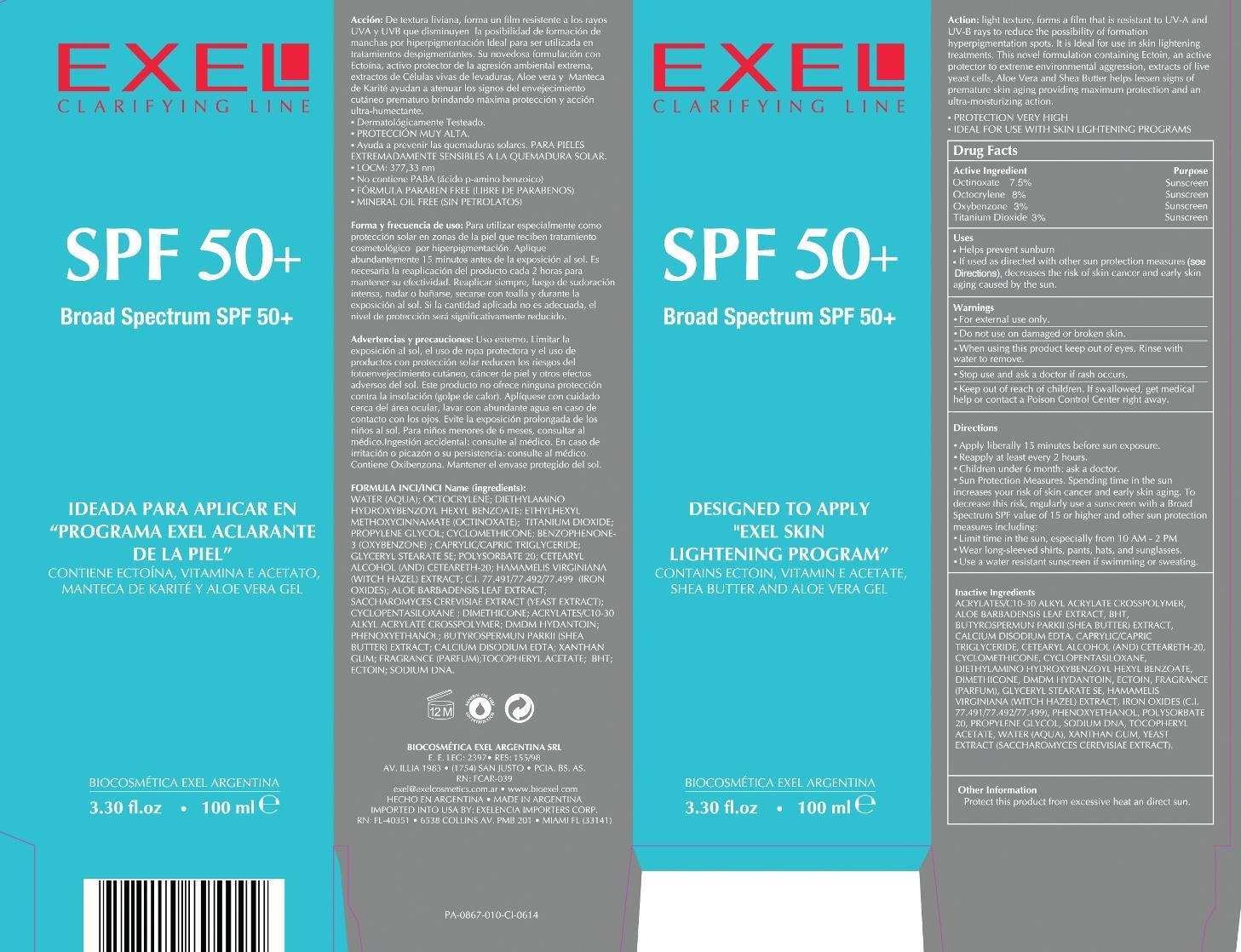 DRUG LABEL: Clarifying Line Broad Spectrum SPF 50
NDC: 53863-124 | Form: CREAM
Manufacturer: Exelencia importers
Category: otc | Type: HUMAN OTC DRUG LABEL
Date: 20150223

ACTIVE INGREDIENTS: OCTINOXATE 7.5 g/100 mL; OCTOCRYLENE 8 g/100 mL; OXYBENZONE 3 g/100 mL; TITANIUM DIOXIDE 3 g/100 mL
INACTIVE INGREDIENTS: CARBOMER INTERPOLYMER TYPE A (ALLYL SUCROSE CROSSLINKED); ALOE VERA LEAF; BUTYLATED HYDROXYTOLUENE; SHEANUT OIL; EDETATE CALCIUM DISODIUM ANHYDROUS; MEDIUM-CHAIN TRIGLYCERIDES; CETOSTEARYL ALCOHOL; POLYOXYL 20 CETOSTEARYL ETHER; CYCLOMETHICONE; CYCLOMETHICONE 5; DIETHYLAMINO HYDROXYBENZOYL HEXYL BENZOATE; DIMETHICONE; DMDM HYDANTOIN; ECTOINE; GLYCERYL STEARATE SE; HAMAMELIS VIRGINIANA TOP; FERRIC OXIDE RED; FERRIC OXIDE YELLOW; FERROSOFERRIC OXIDE; PHENOXYETHANOL; POLYSORBATE 20; PROPYLENE GLYCOL; .ALPHA.-TOCOPHEROL ACETATE; WATER; XANTHAN GUM; YEAST, UNSPECIFIED

Exel Clarifying Line
SPF 50
Broad Spectrum SPF 50

Active Ingredients Purpose

Octinoxate 7.5% .......... Sunscreen

Octocrylene 8% .......... Sunscreen

Oxybenzone 3% .......... Sunscreen

Titanium Dioxide 3% ...... Sunscreen

Uses

- Helps prevent sunburn
- If used as directed with other sun protection measures (see Directions), decreases the risk of skin cancer and early skin aging caused by the sun.

KEEP OUT OF REACH OF CHILDREN

- Keep out reach of children. If swallowed, get medical help or contact a Poison Control Center right away.

- Stop use and ask a doctor if rash occurs

Warnings

- For external use only.
- Do not use on damaged or broken skin.
- When using this product keep out of eyes. Rinse with water to remove

Directions

- Apply liberally 15 minutes before sun exposure
- Reapply at least every 2 hours
- Children under 6 month: ask a doctor
- Sun Protection Measures. Spending time in the sun increases your risk of skin cancer and early skin aging. To decrease this risk, regularly use a sunscreen with a Broad Spectrum SPF value of 15 or higher and other sun protection measures including:
- Limit time in the sun, especially from 10 AM - 2 PM
- Wear long-sleeved shirts, pants, hats, and sunglasses
- Use a water resistanct sunscreen if swimming or sweating

Inactive Ingredients

Acrylates/C10-30 Alkyl Acrylate Crosspolymer, Aloe Barbadensis Leaf Extract, BHT, Butyrospermun Parkii (Shea Butter) Etract, Calcium Disodium EDTA, Caprylic/Capric Triglyceride, Cetaryl Alcohol (and) Ceteareth-20, Cyclomethicone, Cyclopentasiloxane, Diethylamino Hydroxybenzoyl Hexyl Beanzoate, Dimethicone, DMDM Hydantoin, Ectoin, Fragrance (Parfum), Glyceryl Stearate SE, Hamamelis Virginiana (Witch Hazel) Extract, Iron Oxides (C.I. 77.491/77.492/77.499), Phenoxyethanol, Polysorbate 20, Propylene Glycol, Sodium DNA, Tocopheryl Acetate, Water (Aqua), Xanthan Gum, Yeast Extract (Saccharomyces Cerevisiae Extract)

PACKAGE LABEL

SPF 50+

Broa Specturm SPF 50+

Designed to Apply "Exel Skin Lightening Program"

Contains Ectoin, Vitamin E Acetate

3.30 fl.oz . 100 ml